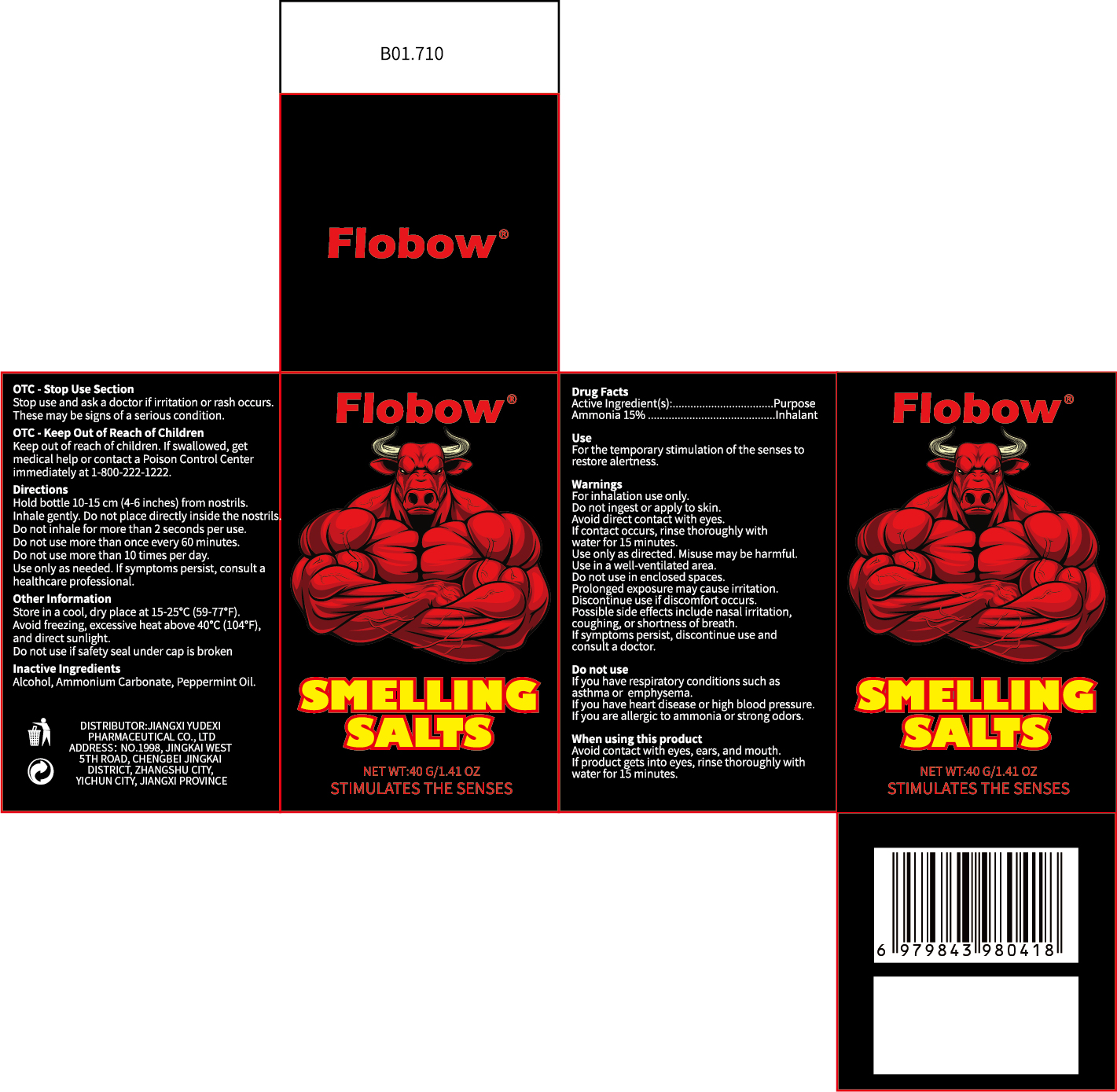 DRUG LABEL: Flobow SMELLING SALTS
NDC: 85248-098 | Form: INHALANT
Manufacturer: Jiangxi Yudexi Pharmaceutical Co., LTD
Category: otc | Type: HUMAN OTC DRUG LABEL
Date: 20260209

ACTIVE INGREDIENTS: AMMONIA 15 g/100 g
INACTIVE INGREDIENTS: AMMONIUM CARBONATE; ALCOHOL; PEPPERMINT OIL

85248-098

Active Ingredient

Ammonia 15%

Purpose

Inhalant

Use

For the temporary stimulation of the senses to restore alertness.

Warnings

For inhalation use only.
Do not ingest or apply to skin.
Avoid direct contact with eyes. If contact occurs, rinse thoroughly with water for 15 minutes.
Use only as directed. Misuse may be harmful.
Use in a well-ventilated area. Do not use in enclosed spaces.
Prolonged exposure may cause irritation. Discontinue use if discomfort occurs.
Possible side effects include nasal irritation, coughing, or shortness of breath. If symptoms persist, discontinue use and consult a doctor.

Do not use

If you have respiratory conditions such as asthma or emphysema.
If you have heart disease or high blood pressure.
If you are allergic to ammonia or strong odors.

When Using

Avoid contact with eyes, ears, and mouth.
If product gets into eyes, rinse thoroughly with water for 15 minutes.

Stop Use

Stop use and ask a doctor if irritation or rash occurs. These may be signs of a serious condition.

Ask Doctor

Stop use and ask a doctor if irritation or rash occurs. These may be signs of a serious condition.

Keep Oot Of Reach Of Children

Keep out of reach of children. If swallowed, get medical help or contact a Poison Control Center immediately at 1-800-222-1222.

Directions

Hold bottle 10-15 cm (4-6 inches) from nostrils.
Inhale gently. Do not place directly inside the nostrils.
Do not inhale for more than 2 seconds per use.
Do not use more than once every 60 minutes.
Do not use more than 10 times per day.
Use only as needed. If symptoms persist, consult a healthcare professional.

Other information

Store in a cool, dry place at 15-25°C (59-77°F).
Avoid freezing, excessive heat above 40°C (104°F), and direct sunlight.
Do not use if safety seal under cap is broken .

Inactive ingredients

Alcohol, Ammonium Carbonate , Peppermint Oil.